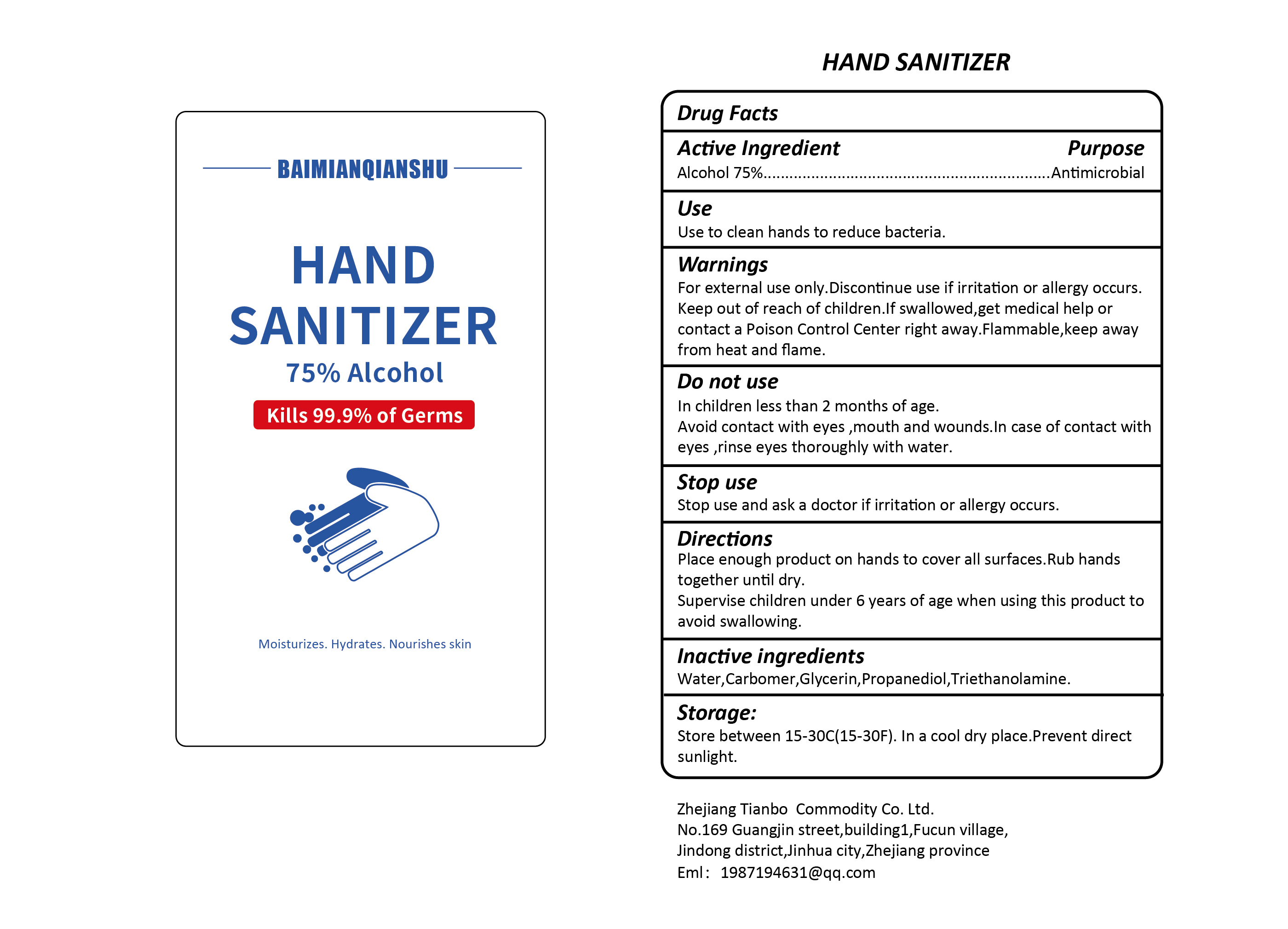 DRUG LABEL: BAIMIANQIANSHU HAND SANITIZER
NDC: 79901-001 | Form: GEL
Manufacturer: Zhejiang Tianbo Daily Necessities Co.Ltd
Category: otc | Type: HUMAN OTC DRUG LABEL
Date: 20200727

ACTIVE INGREDIENTS: ALCOHOL 75 mL/100 mL
INACTIVE INGREDIENTS: PROPANEDIOL; TROLAMINE; CARBOMER INTERPOLYMER TYPE A (55000 CPS); GLYCERIN; WATER

Active Ingredient

Alcohol 75%

Purpose

Antimicrobial

Use

Use to clean hands to reduce bacteria.

Warnings

For external use only. Discontinue use if irritation or allergy occurs. Flammable, keep away from heat and flame.

Keep out of reach of children

If swallowed, get medical help or contact a Poison Control Center right away.

Do not use

In children less than 2 months of age.

Avoid contact with eyes, mouth and wounds. In case of contact with eyes, rinse eyes thoroughly with water.

Stop use

Stop use and ask a doctor if irritation or allergy occurs.

Directions

Place enough product on hands to cover all surfaces. Rub hands together until dry.

Supervise children under 6 years of age when using this product to avoid swallowing.

Inactive ingredients

Water,

Carbomer,

Glycerin,

Propanediol,

Triethanolamine

Storage

Store between 15-30C (15-30F). In a cool dry place. Prevent direct sunlight.